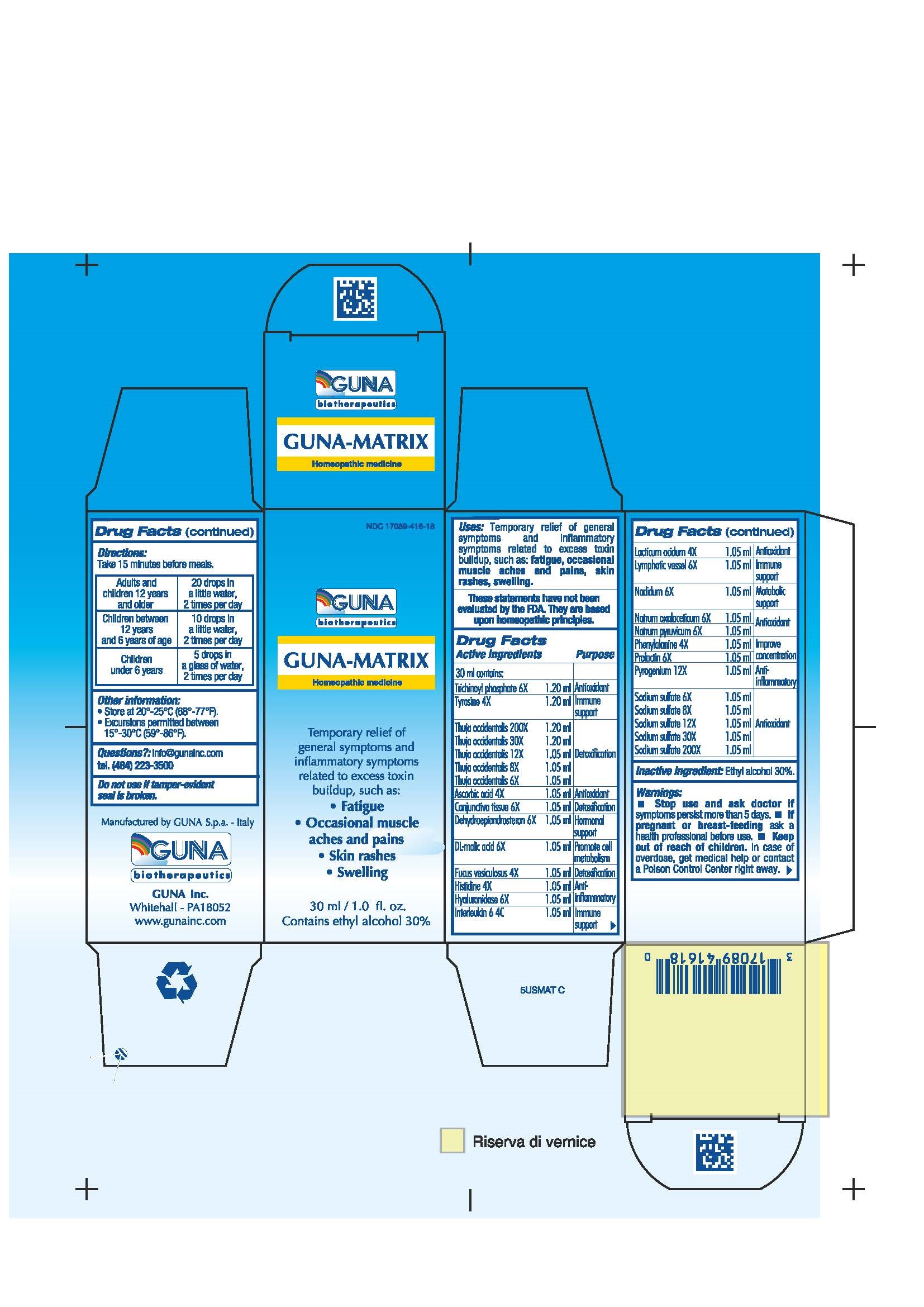 DRUG LABEL: GUNA-MATRIX
NDC: 17089-416 | Form: SOLUTION/ DROPS
Manufacturer: Guna spa
Category: homeopathic | Type: HUMAN OTC DRUG LABEL
Date: 20221115

ACTIVE INGREDIENTS: ASCORBIC ACID 4 [hp_X]/30 mL; SUS SCROFA CONJUNCTIVA 6 [hp_X]/30 mL; PRASTERONE 6 [hp_X]/30 mL; MALIC ACID 6 [hp_X]/30 mL; FUCUS VESICULOSUS 4 [hp_X]/30 mL; HISTIDINE MONOHYDROCHLORIDE 4 [hp_X]/30 mL; HYALURONIDASE 6 [hp_X]/30 mL; HUMAN INTERLEUKIN-6 (NONGLYCOSYLATED) 4 [hp_C]/30 mL; LACTIC ACID, DL- 4 [hp_X]/30 mL; SUS SCROFA SMALL INTESTINE MUCOSA LYMPH FOLLICLE 6 [hp_X]/30 mL; NADIDE 6 [hp_X]/30 mL; SODIUM DIETHYL OXALACETATE 6 [hp_X]/30 mL; SODIUM PYRUVATE 6 [hp_X]/30 mL; SODIUM SULFATE 12 [hp_X]/30 mL; PHENYLALANINE 4 [hp_X]/30 mL; PROLACTIN 6 [hp_X]/30 mL; RANCID BEEF 12 [hp_X]/30 mL; THUJA OCCIDENTALIS LEAFY TWIG 12 [hp_X]/30 mL; DODECAHYDROXYCYCLOHEXANE DIHYDRATE 6 [hp_X]/30 mL; TYROSINE 4 [hp_X]/30 mL
INACTIVE INGREDIENTS: ALCOHOL 9 mL/30 mL

GUNA-MATRIX

ACTIVE INGREDIENTS/PURPOSE

ASCORBIC ACID 4X ANTIOXIDANT
CONJUNCTIVA TISSUE 6X DETOXIFICATION
DEHYDROEPIANDROSTERON 6X HORMONAL SUPPORT
DL-MALIC ACID 6X PROMOTE CELL METABOLISM
FUCUS VESICULOSUS 4X DETOXIFICATION
HISTIDINE 4X ANTI-INFLAMMATORY
HYALURONIDASE 6X ANTI-INFLAMMATORY
INTERLEUKIN 6 4C IMMUNE SUPPORT
LACTICUM ACIDUM 4X ANTIOXIDANT
LYMPHATIC VESSEL 6X IMMUNE SUPPORT
NADIDUM 6X METABOLIC SUPPORT
NATRUM OXALACETICUM 6X ANTIOXIDANT
NATRUM PYRUVICUM 6X ANTIOXIDANT
NATRUM SULPHURICUM 6X, 8X, 12X, 30X, 200X ANTIOXIDANT
PHENYLALANINE 4X IMPROVE CONCENTRATION
PROLACTIN 6X IMPROVE CONCENTRATION
PYROGENIUM 12X ANTI-INFLAMMATORY
THUJA OCCIDENTALIS 6X, 8X, 12X, 30X, 200X DETOXIFICATION
TRICHINOYL PHOSPHATE 6X ANTIOXIDANT
TYROSINE 4X IMMUNE SUPPORT

USES

Temporary Relief of general symptoms and inflammatory symptoms related to excess toxin buildup, such as:

- Fatigue
- Occasionale muscle aches and pains
- Skin rashes
- Swelling

WARNINGS

- Stop use and ask doctor if symptoms persist more than 5 days.
- If pregnant or breast-feeding ask a health professional before use.
- Keep out of reach of children. In case of overdose, get medical help or contact a Poison Control Center right away.
- Contains ethyl alcohol 30%

PREGNANCY

If pregnant or breast-feeding ask a doctor before use

WARNINGS

Keep out of reach of children

DIRECTIONS

Adults and children 12 years and older 20 drops in a little water 2 times per day
Children between 12 years and 6 years of age 10 drops in a little water 2 times per day
Children under 6 years 5 drops in a little water 2 times per day

QUESTIONS

Questions?: info@gunainc.com
Tel. (484) 223-3500

Inactive ingredient: Ethyl alcohol 30%.

INDICATIONS AND USAGE

Take 15 minutes before meals